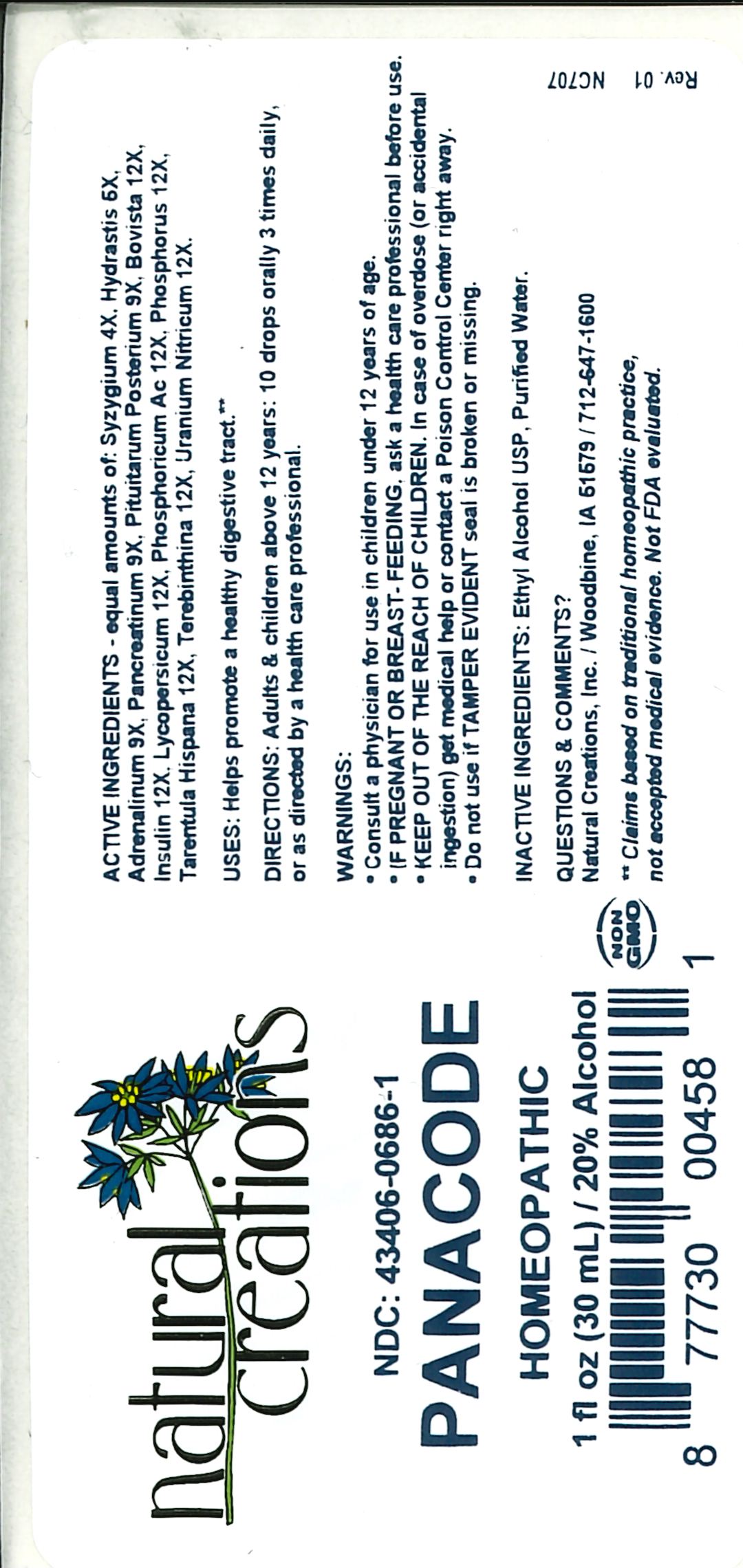 DRUG LABEL: Panacode
NDC: 43406-0686 | Form: LIQUID
Manufacturer: Natural Creations, Inc
Category: homeopathic | Type: HUMAN OTC DRUG LABEL
Date: 20251216

ACTIVE INGREDIENTS: SYZYGIUM CUMINI SEED 4 [hp_X]/1 mL; GOLDENSEAL 6 [hp_X]/1 mL; EPINEPHRINE 9 [hp_X]/1 mL; PANCRELIPASE 9 [hp_X]/1 mL; SUS SCROFA PITUITARY GLAND, POSTERIOR 9 [hp_X]/1 mL; LYCOPERDON UTRIFORME FRUITING BODY 12 [hp_X]/1 mL; INSULIN PORK 12 [hp_X]/1 mL; SOLANUM LYCOPERSICUM WHOLE 12 [hp_X]/1 mL; PHOSPHORIC ACID 12 [hp_X]/1 mL; PHOSPHORUS 12 [hp_X]/1 mL; LYCOSA TARANTULA 12 [hp_X]/1 mL; TURPENTINE OIL 12 [hp_X]/1 mL; URANYL NITRATE HEXAHYDRATE 12 [hp_X]/1 mL
INACTIVE INGREDIENTS: ALCOHOL; WATER

Panacode

ACTIVE INGREDIENT

ACTIVE INGREDIENTS - equal amounts of: Syzygium 4X, Hydrastis 6X, Adrenalinum 9X, Pancreatinum 9X, Pituitarum Posterium 9X, Bovista 12X, Insulin 12X, Lycopersicum 12X, Phosphoricum Ac 12X, Phosphorus 12X, Tarentula Hispana 12X, Terebinthina 12X, Uranium Nitricum 12X

INDICATIONS AND USAGE

USES: Helps promote a healthy digestive tract.**

PURPOSE

USES: Helps promote a healthy digestive tract.**

DOSAGE AND ADMINISTRATION

DIRECTIONS: Adults & children above 12 years: 10 drops orally 3 times daily, or as directed by a health care professional.

KEEP OUT OF REACH OF CHILDREN

KEEP OUT OF THE REACH OF CHILDREN. In case of overdose (or accidental ingestion) get medical help or contact a Poison Control Center right away.

WARNINGS:

- Consult a physician for use in children under 12 years of age.
- IF PREGNANT OR BREAST-FEEDING, ask a health care professional before use.
- KEEP OUT OF THE REACH OF CHILDREN. In case of overdose (or accidental ingestion) get medical help or contact a Poison Control Center right away.
- Do not use if TAMPER EVIDENT seal is broken or missing.

INACTIVE INGREDIENTS: Ethyl Alcohol USP, Purified Water

QUESTIONS & COMMENTS?

Natural Creations, Inc. / Woodbine, IA 51579 / 712-647-1600

REFERENCES

**Claims based on traditional homeopathic practice, not accepted medical evidence. Not FDA evaluated.

PACKAGE LABEL

NDC:43406-0686-1

Panacode

HOMEOPATHIC

1 fl oz (30mL) / 20% Alcohol